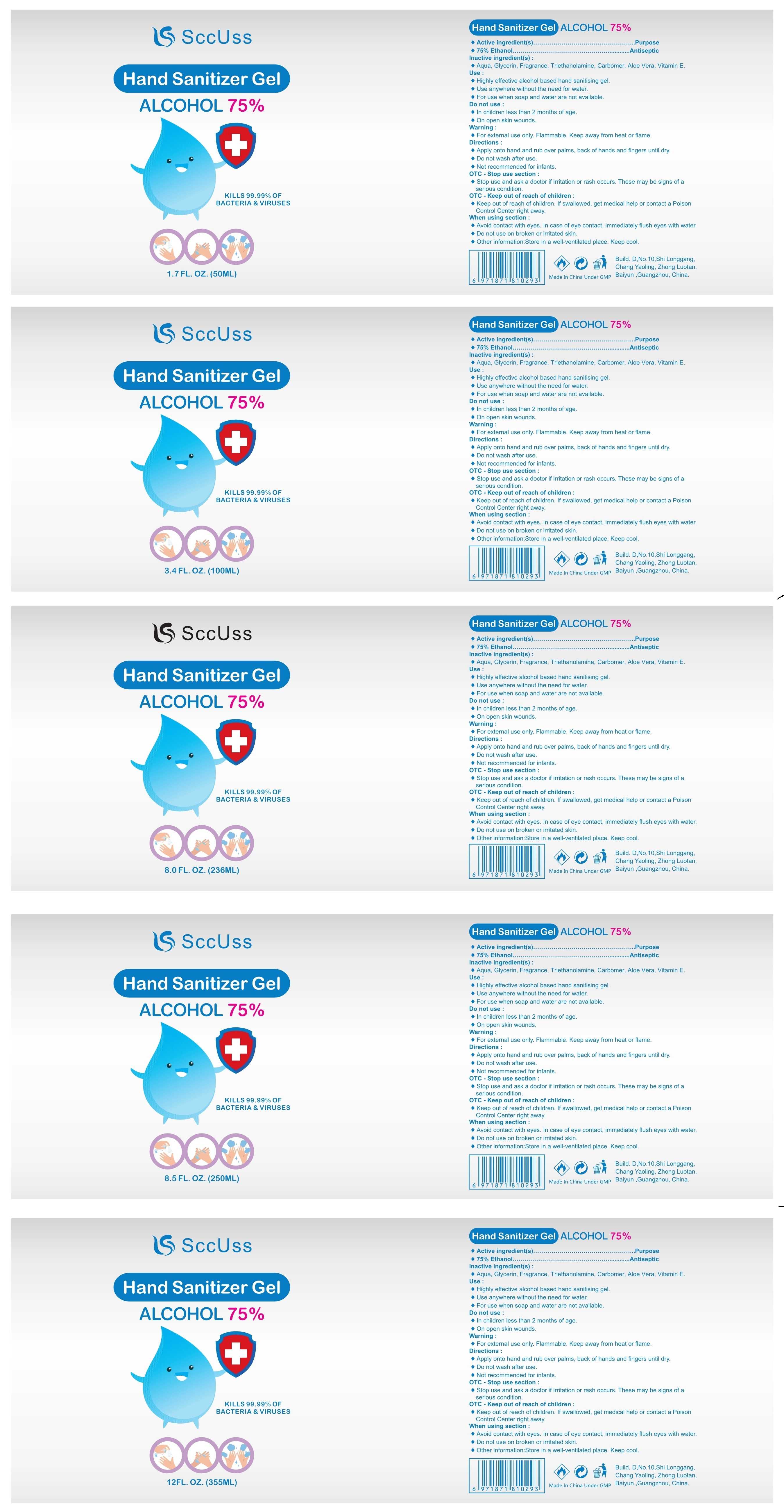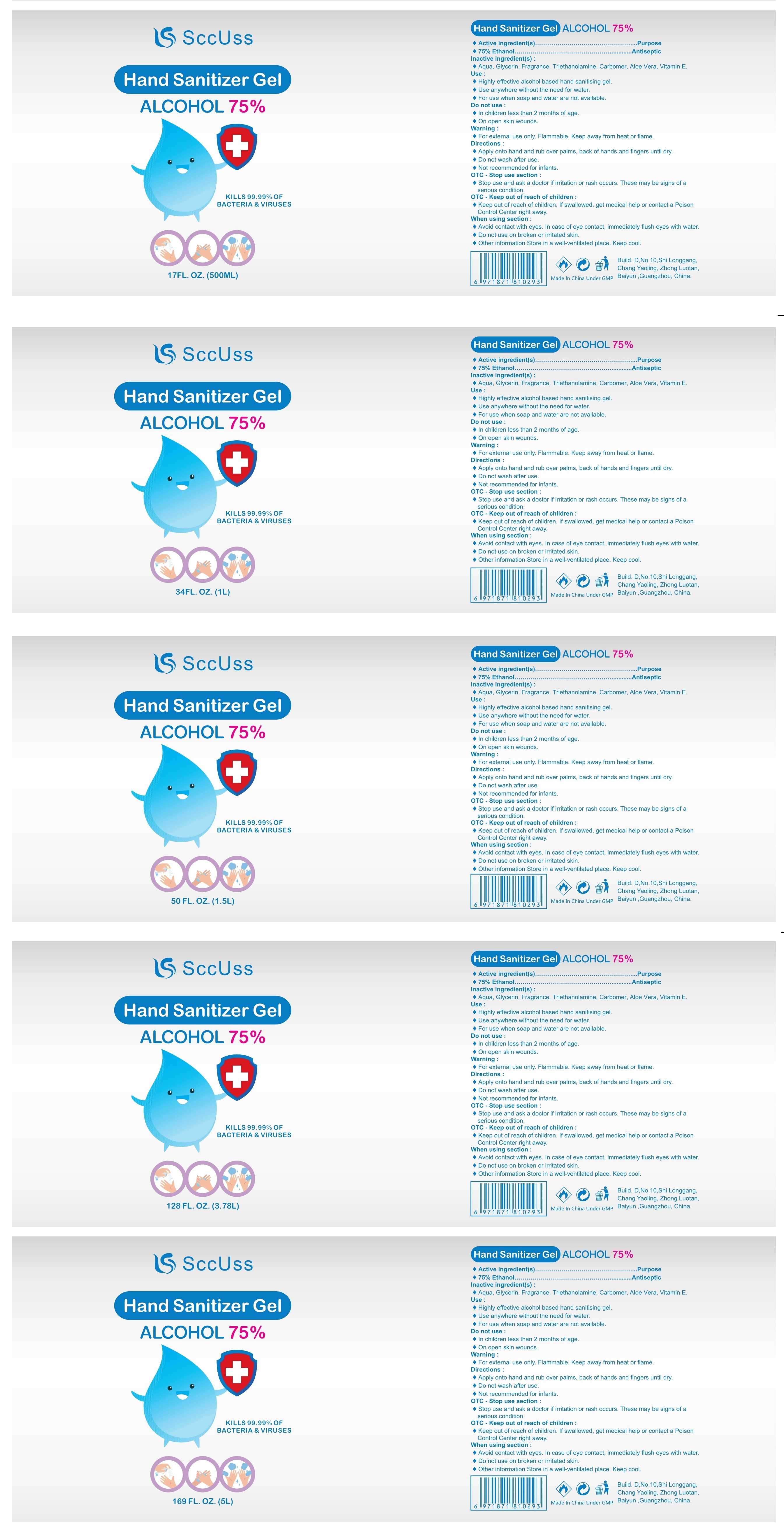 DRUG LABEL: SccUss Hand Sanitizer Gel
NDC: 80035-001 | Form: GEL
Manufacturer: Guangzhou AOCAI Bio-Technology Co., Ltd.
Category: otc | Type: HUMAN OTC DRUG LABEL
Date: 20200810

ACTIVE INGREDIENTS: ALCOHOL 75 mL/100 mL
INACTIVE INGREDIENTS: ALOE VERA LEAF; .ALPHA.-TOCOPHEROL; FRAGRANCE GREEN APPLE ORC2001072; CARBOMER HOMOPOLYMER, UNSPECIFIED TYPE; GLYCERIN; TROLAMINE; WATER

001 SccUss Hand Sanitizer Gel

Active Ingredient(s)

75% Ethanol

Purpose

Antiseptic

Use

Highly effective alcohol based hand sanitising gel.
Use anywhere without the need for water.
For use when soap and water are not available.

Warnings

For external use only. Flammable. Keep away from heat or flame.

Do not use

In children less than 2 months of age.
On open skin wounds.

WHEN USING

Avoid contact with eyes. In case of eye contact, immediately flush eyes with water.
Do not use on broken or irritated skin.

Stop use and ask a doctor if irritation or rash occurs. These may be signs of a serious condition.

Keep out of reach of children. If swallowed, get medical help or contact a Poison Control Center right away.

Directions

Apply onto hand and rub over palms, back of hands and fingers until dry.
Do not wash after use.
Not recommended for infants.

Other information

Store in a well-ventilated place. Keep cool.

Inactive ingredients

Aqua, Glycerin, Fragrance, Triethanolamine, Carbomer, Aloe Vera, Vitamin E.